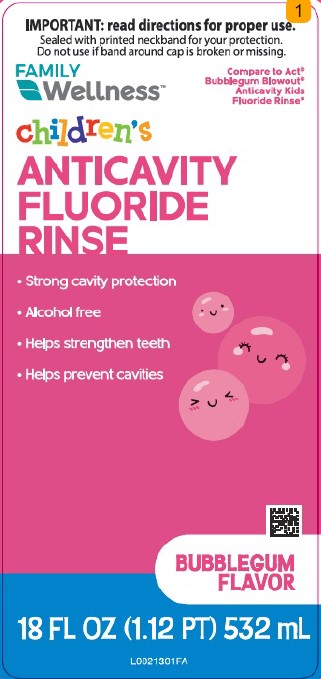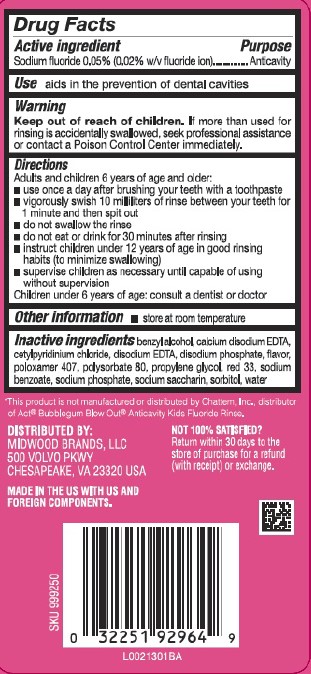 DRUG LABEL: Anticavity Rinse
NDC: 55319-004 | Form: MOUTHWASH
Manufacturer: Family Dollar Stores, Inc
Category: otc | Type: HUMAN OTC DRUG LABEL
Date: 20260224

ACTIVE INGREDIENTS: SODIUM FLUORIDE 0.2 mg/1 mL
INACTIVE INGREDIENTS: BENZYL ALCOHOL; EDETATE CALCIUM DISODIUM ANHYDROUS; CETYLPYRIDINIUM CHLORIDE; EDETATE DISODIUM; SODIUM PHOSPHATE, DIBASIC, ANHYDROUS; POLOXAMER 407; POLYSORBATE 80; PROPYLENE GLYCOL; D&C RED NO. 33; SODIUM BENZOATE; SODIUM PHOSPHATE; SACCHARIN SODIUM; SORBITOL; WATER

Family Wellness 004.002/004AE
Anticavity Fluoride Rinse, Bubble Gum

Active ingredient

Sodium Fluoride 0.05% (0.02% w/v fluoride ion)

Purpose

Anticavity

Use

aids in the prevention of dental cavities

Warnings

for this product

Keep out of reach of children.

If more than used for rinsing is accidentally swallowed, seek professional assistance or contact a Poison Control Center immediately.

Directions

Adults and children 6 year of age and older:

- use once a day after brushing your teeth with a toothpaste
- vigorously swish 10 milliliters of rinse between your teeth for 1 minute and then spit out
- do not swallow the rinse
- do not eat or drink for 30 minutes after rinsing
- instruct children under 12 years of age in good rinsing habits (to minimize swallowing)
- supervise children as necessary until capable of using without supervision

Children under 6 year of age: consult a dentist or doctor

Other information

- store at room temperature

Inactive ingredients

benzyl alcohol, calcium disodium EDTA, cetylpyridinium chloride, disodium EDTA, disodium phosphate, flavor, poloxamer 407, polysorbate 80, propylene glycol, red 33, sodium benzoate, sodium phosphate, sodium saccharin, sorbitol, water

Disclaimer

*This product is not manufactured or distributed by Chattem, Inc., distributor of Act® Bubblegum Blow Out® Anticavity Kids Fluoride Rinse.

Adverse reaction

DISTRIBUTED BY:

MIDWOOD BRANDS, LLC

500 VOLVO PKWY

CHESAPEAKE, VA 23320 USA

NOT 100% SATISFIED?

Return within 30 days to the store of purchase for a refund (with receipt) or exchange.

MADE IN THE US WITH US AND FOREIGN COMPONENTS

Principal display panel

IMPORTANT: read directions for proper use.

Sealed with printed neckband for your protection.

Do not use if band around cap is broken or missing.

FAMILY WELLNESS™

Compare to ACT® Bubblegum Blowout® Anticavity Kids Fluoride Rinse*

Children's ANTICAVITY FLUORIDE RINSE

- Strong cavity protection
- Alcohol free
- Helps strengthen teeth
- Helps prevent cavities

BUBBLEGUM FLAVOR

18 FL OZ (1.12 PT) 532 mL